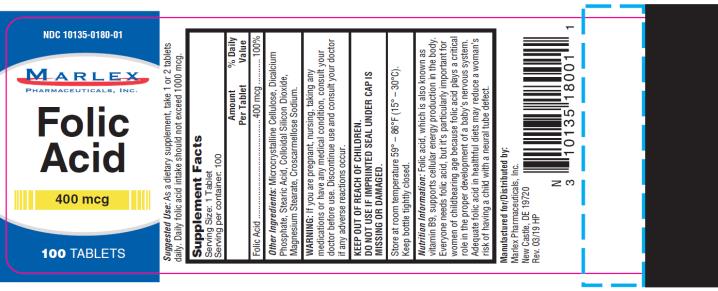 DRUG LABEL: Folic Acid
NDC: 10135-180 | Form: TABLET
Manufacturer: Marlex Pharmaceuticals Inc
Category: other | Type: DIETARY SUPPLEMENT
Date: 20190313

ACTIVE INGREDIENTS: FOLIC ACID 400 ug/1 1
INACTIVE INGREDIENTS: MICROCRYSTALLINE CELLULOSE; ANHYDROUS DIBASIC CALCIUM PHOSPHATE; CROSCARMELLOSE SODIUM; STEARIC ACID; MAGNESIUM STEARATE; SILICON DIOXIDE

Folic Acid 400mcg

Suggested Use:

As a dietary supplement, take 1 or 2 tablets daily. Daily folic acid intake should not exceed 1000mcg.

Supplement Facts

Serving Size: 1 Tablet

Serving per container: 100

Amount Per Tablet %Daily Value

Folic Acid………………………………….400mcg………………………………100%

OTHER INGREDIENTS:

Microcrystalline Cellulose, Dicalcium Phosphate, Stearic Acid, Colloidal Silicon Dioxide, Magnesium Stearate, Croscarnellouse Sodium

WARNING:

If you are pregnant, nursing, taking any medications or have any medical condition, consult your doctor before use. Discontinue use and consult your doctor if any adverse reactions occurs.

KEEP OUT OF REACH OF CHILDREN. DO NOT USE IF IMPRINTED SEAL UNDER CAP IS MISSING OR DAMAGED.

- Store at room temperature 59° - 86° (15° - 30°)
- Keep bottle tightly closed.

Nutrition Information: Folic acid, which is also known as vitamin B9, supports cellular energy productions in the body. Everyone needs folic acid, but it’s particularly important for the women of childbearing age because folic acid plays a critical role in the proper develop of the baby’s nervous system. Adequate folic acid in healthful diets may reduce a woman’s risk of having a child with a neural tube defect.

Manufactured for/Distributed by:

Marlex Pharmaceuticals, Inc.

New Castle, DE 19720

Rev. 03/19 HP

PRINCIPAL DISPLAY PANEL

NDC 10135-0180-01
Folic Acid
400 mcg
100 TABLETS